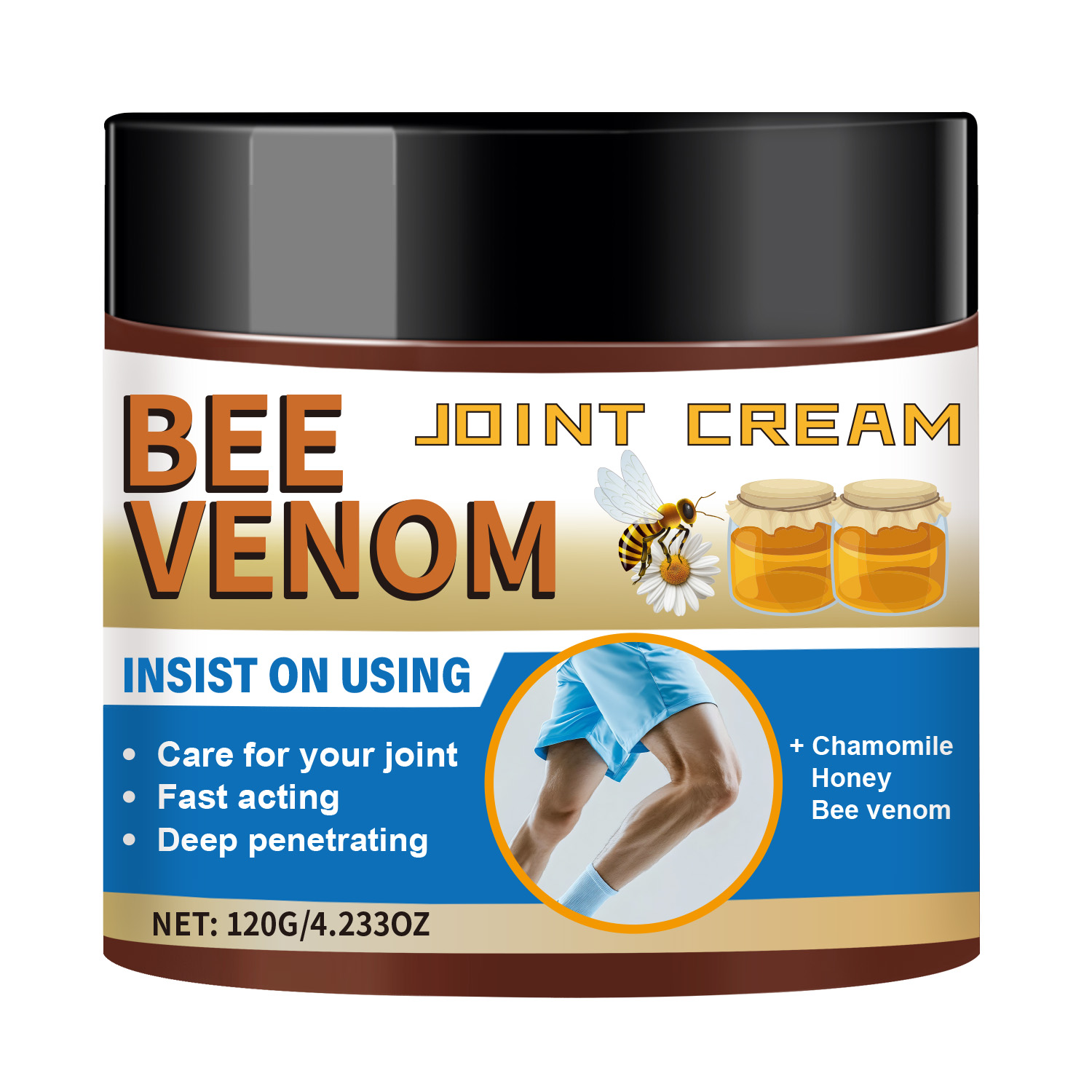 DRUG LABEL: Bee Venom Joint Cream
NDC: 84025-326 | Form: CREAM
Manufacturer: Guangzhou Yanxi Biotechnology Co., Ltd
Category: otc | Type: HUMAN OTC DRUG LABEL
Date: 20250830

ACTIVE INGREDIENTS: POLYSORBATE 60 3 mg/120 g; GLYCERIN 4 mg/120 g
INACTIVE INGREDIENTS: WATER

DOSAGE AND ADMINISTRATION

Use as a Normal Skin Cream

WARNINGS

Keep out of children

INACTIVE INGREDIENT

Aqua

INDICATIONS AND USAGE

For daily skin care

Keep out of children

PURPOSE

Moisturizing